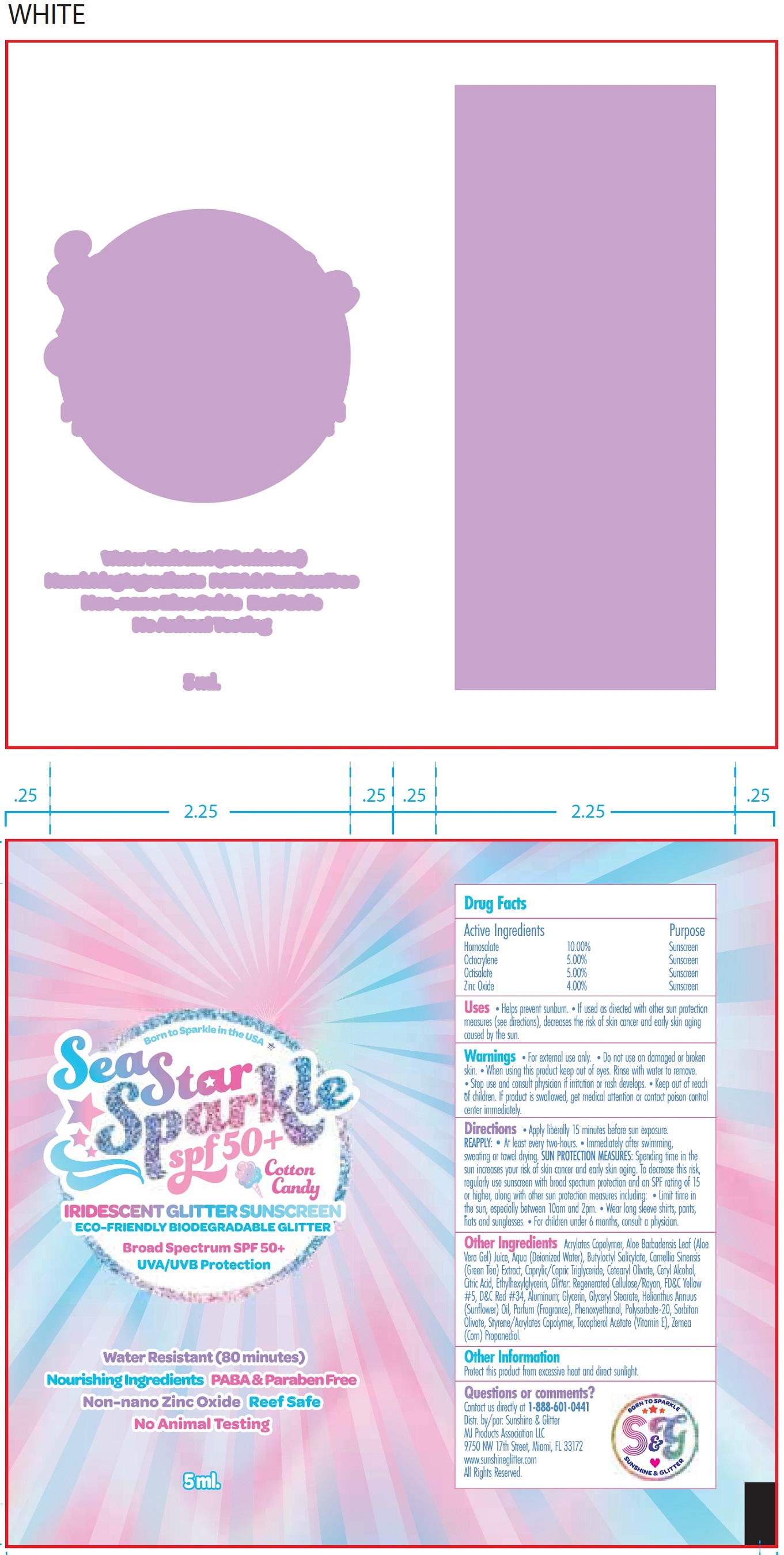 DRUG LABEL: SEA STAR SPARKLE SPF 50 Glitter Sunscreen Cotton Candy
NDC: 72085-307 | Form: CREAM
Manufacturer: MJ Products Association, LLC
Category: otc | Type: HUMAN OTC DRUG LABEL
Date: 20231105

ACTIVE INGREDIENTS: HOMOSALATE 100 mg/1 mL; OCTOCRYLENE 50 mg/1 mL; OCTISALATE 50 mg/1 mL; ZINC OXIDE 40 mg/1 mL
INACTIVE INGREDIENTS: ALOE VERA LEAF; WATER; BUTYLOCTYL SALICYLATE; GREEN TEA LEAF; MEDIUM-CHAIN TRIGLYCERIDES; CETEARYL OLIVATE; CETYL ALCOHOL; CITRIC ACID MONOHYDRATE; ETHYLHEXYLGLYCERIN; REGENERATED CELLULOSE; FD&C YELLOW NO. 5; D&C RED NO. 34; ALUMINUM; GLYCERIN; GLYCERYL MONOSTEARATE; HELIANTHUS ANNUUS FLOWERING TOP; PHENOXYETHANOL; POLYSORBATE 20; SORBITAN OLIVATE; .ALPHA.-TOCOPHEROL ACETATE; CORN; PROPANEDIOL

SEA STAR SPARKLE SPF-50 Glitter Sunscreen Cotton Candy

Active Ingredients

Homosalate 10.00%

Octocrylene 5.00%

Octisalate 5.00%

Zinc Oxide 4.00%

Purpose

Sunscreen

Uses

- Helps prevent sunburn.
- If used as directed with other sun protection measures (see directions), decreases the risk of skin cancer and early skin aging caused by the sun.

Warnings

For external use only.

Do not use

- on damaged or broken skin.

When using this product

keep out of eyes. Rinse with water to remove.

Stop use and consult physician

if irritation or rash develops.

Keep out of reach of children.

If product is swallowed, get medical attention or contact poison control center immediately.

Directions

- Apply liberally 15 minutes before sun exposure.

- At least every two-hours.
- Immediately after swimming, sweating or towel drying. Spending time in the sun increases your risk of skin cancer and early skin aging. To decrease this risk, regularly use suncreen with broad spectrum protection and on SPF rating of 15 or higher, along with other sun protection measures including: Limit time in the sun, especially between 10am and 2pm. SUN PROTECTION MEASURES:
- Wear long sleeve shirts, pants, hats, and sunglasses.
- For children under 6 months, consult a physician.

REAPPLY:

Other Ingredients

Acrylate Copolymer, Aloe Barbadensis Leaf (Aloe Vera Gel), Juice, Aqua (Deionized Water), Butyloctyl Salicylate, Camellia Sinensis (Green Tea), Extract, Caprylic/Capric Triglyceride, Cetearyl Olivate, Cetyl Alcohol, Citric Acid, Ethylhexylglycerin, Glitter: Regenerated Cellulose/Rayon, FD&C Yellow #5, D&C Red 34, Aluminium; Glycerin, Glyceryl Stearate, Helianthus Annuus (Sunflower) Oil, Parfum (Fragrance), Phenoxyethanol, Polysorbate-20, Sorbitan Olivate, Styrene/Acrylates Copolymer, Tocopherol Acetate (Vitamin E), Zemea (Corn) Propanediol.

Other Information

Protect this product from excessive heat and direct sunlight.

Questions or comments?

Contact us directly at 1-888-601-0441